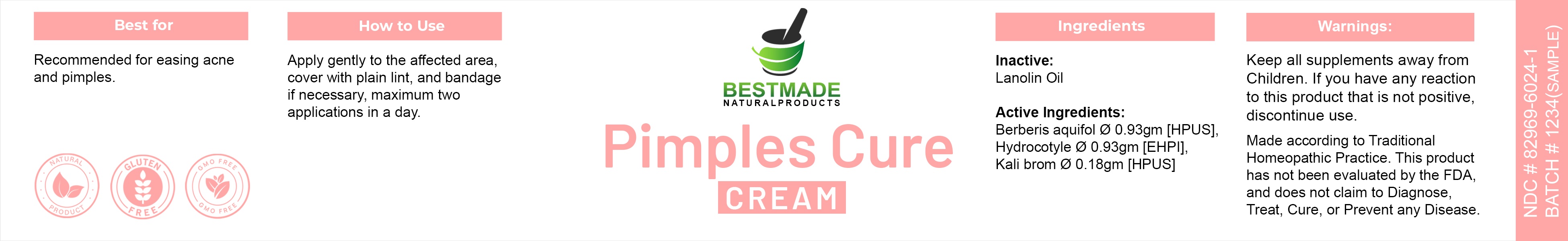 DRUG LABEL: Bestmade Natural Products Pimples Cure Cream
NDC: 82969-6024 | Form: OINTMENT
Manufacturer: Bestmade Natural Products
Category: homeopathic | Type: HUMAN OTC DRUG LABEL
Date: 20250102

ACTIVE INGREDIENTS: POTASSIUM BROMIDE 0.18 g/40 g; CENTELLA ASIATICA WHOLE 0.93 g/40 g; BERBERIS AQUIFOLIUM ROOT BARK 0.93 g/40 g
INACTIVE INGREDIENTS: LANOLIN OIL 40 g/40 g

Pimples Cure Cream

DOSAGE AND ADMINISTRATION

Apply gently to the arrected area cover with plain lint, and bandage If necessary, maximum two applications in a day.

INDICATIONS AND USAGE

Best for

Recommend for easing acne and pimples.

Inactive Ingredient

Lanolin Oil

Active Ingredients

Berberis aquifol Ø 0.93gm [HPUS]
Hydrocotyle Ø 0.93gm [HPUS]
Kali brom Ø 0.18gm [HPUS]

Warnings:

Keep all supplements away from Children.

If you have any reaction to this product that is not positive, discontinue use.

Made according to Traditional Homeopathic Practice. This product has not been evaluated by the FDA and does not claim to Diagnose, Treat, Cure, or Prevent any Disease.

PURPOSE

Best for

Recommend for easing acne and pimples.

Warnings:

Keep all supplements away from Children.

If you have any reaction to this product that is not positive, discontinue use.

Made according to Traditional Homeopathic Practice. This product has not been evaluated by the FDA and does not claim to Diagnose, Treat, Cure, or Prevent any Disease.

Entire package label